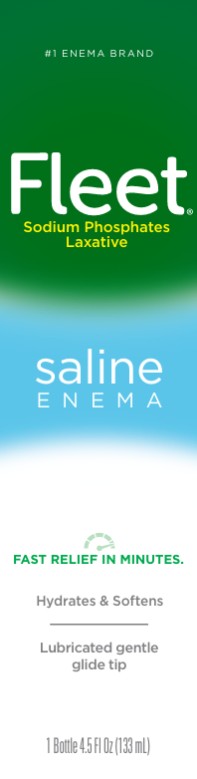 DRUG LABEL: Fleet
NDC: 0132-0201 | Form: ENEMA
Manufacturer: C.B. Fleet Company, Inc.
Category: otc | Type: HUMAN OTC DRUG LABEL
Date: 20251120

ACTIVE INGREDIENTS: SODIUM PHOSPHATE, DIBASIC, HEPTAHYDRATE 7 g/118 mL; SODIUM PHOSPHATE, MONOBASIC 19 g/118 mL
INACTIVE INGREDIENTS: EDETATE DISODIUM; WATER; BENZALKONIUM CHLORIDE

Fleet Saline Enema 0132-0201

Active Ingredient (in each 118 mL delivered dose)

Monobasic Sodium Phosphate 19 g................

Dibasic Sodium Phosphate 7 g........................

Purpose

Saline laxative

Saline laxative

Use

for relief of occasional constipation. This product usually produces a bowel movement in 1 to 5 minutes.

Warnings

Using more than one enema in 24 hours can be harmful.

For rectal use only.

Do not use

- for more than 3 days
- if you have kidney disease
- if you have heart problems
- if you are dehydrated
- when abdominal pain, nausea, or vomiting are present unless directed by a doctor

Ask a doctor before using this product if you

- are 55 years of age or older
- are on a sodium-restricted diet
- have a sudden change in bowel habits lasting more than 2 weeks
- already used a laxative for more than 1 week

Stop use and ask a doctor if you have

- rectal bleeding
- no bowel movement or no liquid comes out of the rectum after 30 minutes
- symptoms of dehydration [feeling thirsty, dizziness, vomiting, urinating less often than normal]

These symptoms may indicate a serious condition.

If pregnant or breast-feeding,

ask a health professional before use.

Keep out of reach of children.

If swallowed, get medical help or contact a Poison Control Center right away.

Directions

Single Daily Dosage (per 24 hours)
Do not use if taking another sodium phosphates product.
Do not use more unless directed by a doctor. See Warnings.
adults and children 12 years and over 1 bottle per day
children 2 to 11 yearsuse Fleet® Pedia-Lax® Enema
children under 2 yearsDO NOT USE
If no urge is felt after 5 minutes of using, try to empty bowel. Call a doctor promptly if no liquid comes out of the rectum after 30 minutes because dehydration could occur.

Other Information

- each 118 mL delivered dose contains: sodium 4.4 g
- additional liquids by mouth are recommended while taking this product

Inactive Ingredients

benzalkonium chloride, disodium EDTA, purified water

Questions?

1-866-255-6960 or www.fleetlabs.com

Tamper Evident: Bottle sealed for safety. If bottle wrapper with Fleet® emblem is torn, damaged or missing, do not use.

PRINCIPAL DISPLAY PANEL

Fleet ®
Laxative
Saline Enema
1 Bottle 4.5 Fl Oz (133 mL)